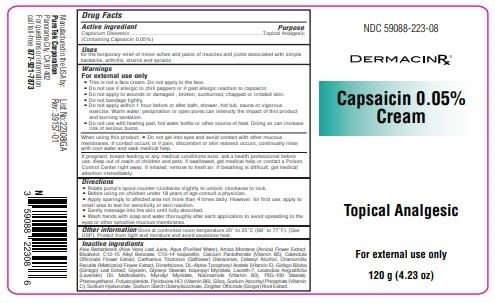 DRUG LABEL: Capsaicin 0.05% Cream
NDC: 59088-223 | Form: CREAM
Manufacturer: Puretek Corporation
Category: otc | Type: HUMAN OTC DRUG LABEL
Date: 20250228

ACTIVE INGREDIENTS: CAPSICUM OLEORESIN 0.5 mg/1 g
INACTIVE INGREDIENTS: CALENDULA OFFICINALIS FLOWER; CETEARYL ALCOHOL; PHENOXYETHANOL; SILICA; ARNICA MONTANA FLOWER; CARTHAMUS TINCTORIUS (SAFFLOWER) OLEOSOMES; MYRISTYL MYRISTATE; NIACINAMIDE; GLYCERIN; PEG-100 STEARATE; ALUMINUM STARCH OCTENYLSUCCINATE; GINGER; SODIUM HYALURONATE; BISABOLOL; MALTODEXTRIN; AQUA; GINKGO BILOBA LEAF; ISOPROPYL MYRISTATE; LAURETH-7; LAVANDULA ANGUSTIFOLIA (LAVENDER) OIL; C13-14 ISOPARAFFIN; CALCIUM PANTOTHENATE; SODIUM ASCORBYL PHOSPHATE; PYRIDOXINE HCL; C12-15 ALKYL BENZOATE; ACRYLAMIDE/SODIUM ACRYLOYLDIMETHYLTAURATE COPOLYMER (120000 MPA.S AT 1%); ALOE VERA LEAF; CHAMOMILE; DIMETHICONE; .ALPHA.-TOCOPHEROL ACETATE, DL-; GLYCERYL STEARATE

Capsaicin 0.05% Cream

Active ingredient

Capsicum Oleoresin (Containing Capsaicin 0.05%)

Purpose

Topical Analgesic

Uses

for the temporary relief of minor aches and pains of muscles and joints associated with simple backache, arthritis, strains and sprains

Warnings

For external use only
• This is not a face cream. Do not apply to the face.
• Do not use if allergic to chili peppers or if past allergic reaction to capsaicin.
• Do not apply to wounds or damaged , broken, sunburned, chapped or irritated skin.
• Do not bandage tightly.
• Do not apply within 1 hour before or after bath, shower, hot tub, sauna or vigorous
exercise. Warm water, perspiration or open pores can intensify the impact of this product
and burning sentation.
• Do not use with heating pad, hot water bottle or other source of heat. Doing so can increase
risk of serious burns.

When using this product

• Do not get into eyes and avoid contact with other mucous membranes. If contact occurs or if pain, discomfort or skin redness occurs, continually rinse with cool water and seek medical help.

KEEP OUT OF REACH OF CHILDREN

If pregnant, breast-feeding or any medical conditions exist, ask a health professional before use. Keep out of reach of children and pets. if swallowed, get medical help or contact a Poison Control Center right away. If inhaled, remove to fresh air. If breathing is difficult, get medical attention immediately.

Directions

• Rotate pump’s spout counter-clockwise slightly to unlock; clockwise to lock.
• Before using on children under 18 years of age consult a physician.
• Apply sparingly to affected area not more than 4 times daily. However, for first use, apply to
small area to test for sensitivity or skin reaction.
• Gently massage into the skin until fully absorbed.
• Wash hands with soap and water thoroughly after each application to avoid spreading to the
eyes or other sensitive mucous membranes.

Other Information

Store at controlled room temperature 20° to 25°C (68° to 77°F). [See USP]. Protect from light and moisture and avoid excessive heat.

Inactive ingredients

Aloe Barbadensis (Aloe Vera) Leaf Juice, Aqua (Purified Water), Arnica Montana (Arnica) Flower Extract, Bisabolol, C12-15 Alkyl Benzoate, C13-14 Isoparaffin, Calcium Pantothenate (Vitamin B5), Calendula Officinalis Flower Extract, Carthamus Tinctorius (Safflower) Oleosomes, Cetearyl Alcohol, Chamomilla Recutita (Matricaria) Flower Extract, Dimethicone, DL-Alpha-Tocopheryl Acetate (Vitamin E), Ginkgo Biloba (Ginkgo) Leaf Extract, Glycerin, Glyceryl Stearate, Isopropyl Myristate, Laureth-7, Lavandula Angustifolia (Lavender) Oil, Maltodextrin, Myristyl Myristate, Niacinamide (Vitamin B3), PEG-100 Stearate, Phenoxyethanol, Polyacrylamide, Pyridoxine HCl (Vitamin B6), Silica, Sodium Ascorbyl Phosphate (Vitamin C), Sodium Hyaluronate, Sodium Starch Octenylsuccinate, Zingiber Officinale (Ginger) Root Extract.

Label

Manufactured in the USA by:
PureTek Corporation
Panorama City, CA 91402
For questions or information
call toll-free: 877-921-7873